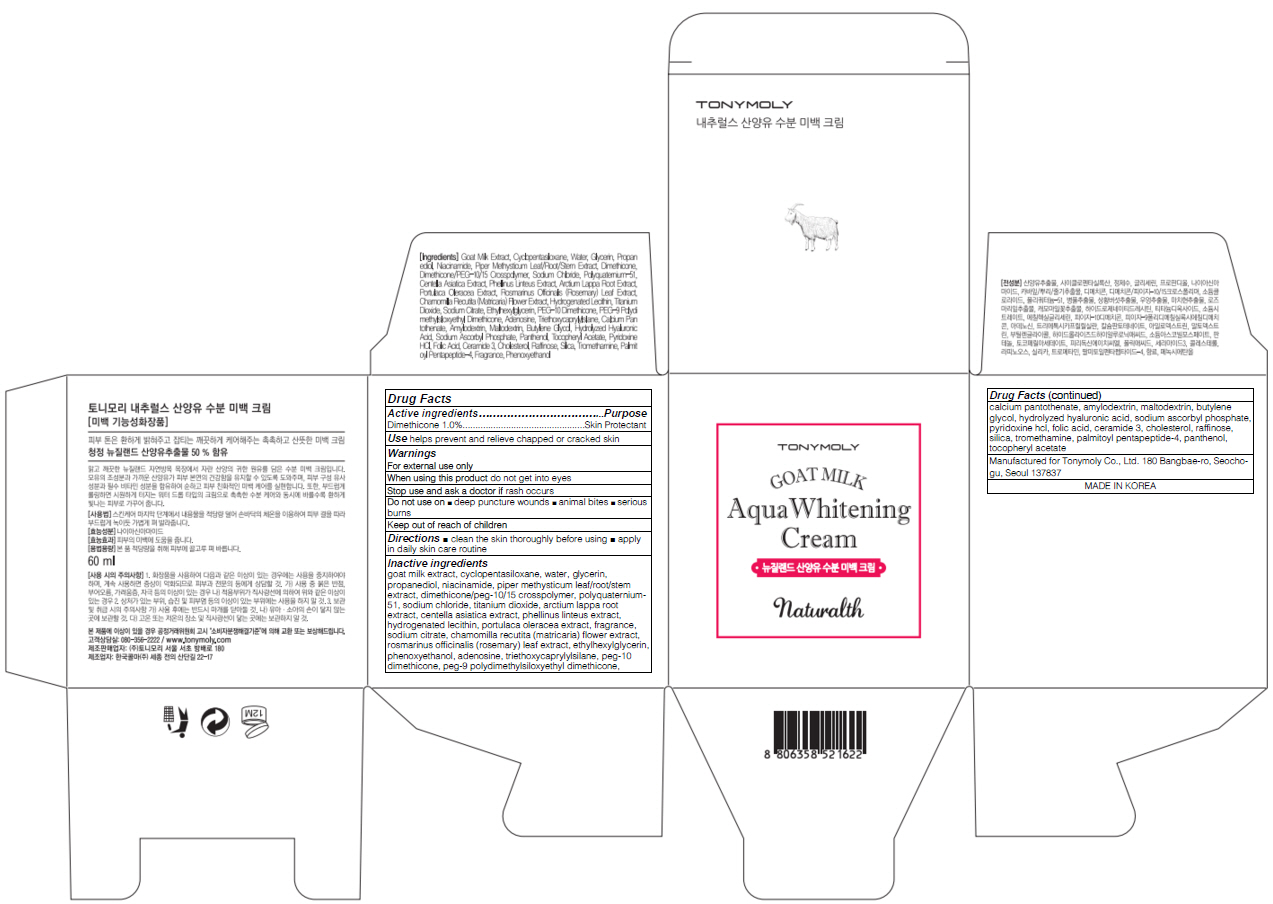 DRUG LABEL: TONYMOLY NATURALTH GOAT MILK AQUA WHITENING
NDC: 59078-270 | Form: CREAM
Manufacturer: TONYMOLY CO.,LTD
Category: otc | Type: HUMAN OTC DRUG LABEL
Date: 20160122

ACTIVE INGREDIENTS: Dimethicone 0.6 g/60 mL
INACTIVE INGREDIENTS: goat milk; water

ACTIVE INGREDIENT

Active ingredients: Dimethicone 1.0%

INACTIVE INGREDIENT

Inactive ingredients: goat milk extract, cyclopentasiloxane, water, glycerin, propanediol, niacinamide, piper methysticum leaf/root/stem extract, dimethicone/peg-10/15 crosspolymer, polyquaternium-51, sodium chloride, titanium dioxide, arctium lappa root extract, centella asiatica extract, phellinus linteus extract, hydrogenated lecithin, portulaca oleracea extract, fragrance, sodium citrate, chamomilla recutita (matricaria) flower extract, rosmarinus officinalis (rosemary) leaf extract, ethylhexylglycerin, phenoxyethanol, adenosine, triethoxycaprylylsilane, peg-10 dimethicone, peg-9 polydimethylsiloxyethyl dimethicone, calcium pantothenate, amylodextrin, maltodextrin, butylene glycol, hydrolyzed hyaluronic acid, sodium ascorbyl phosphate, pyridoxine hcl, folic acid, ceramide 3, cholesterol, raffinose, silica, tromethamine, palmitoyl pentapeptide-4, panthenol, tocopheryl acetate

PURPOSE

Purpose: Skin Protectant

WARNINGS

Warnings: For external use only

When using this product do not get into eyes

Stop use and ask a doctor if rash occurs

Do not use on - deep puncture wounds - animal bites - serious burns

Keep out of reach of children

KEEP OUT OF REACH OF CHILDREN

Use

Use: helps prevent and relieve chapped or cracked skin

Directions

Directions: - clean the skin thoroughly before using - apply in daily skin care routine